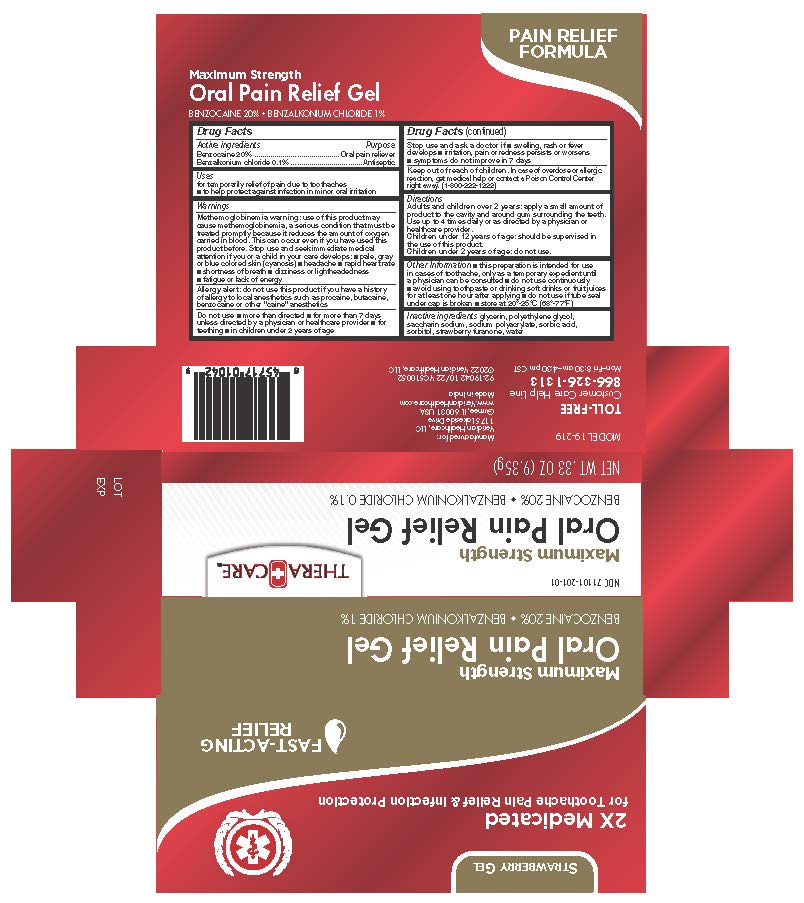 DRUG LABEL: TheraCare Maximum Strength Oral Pain Relief
NDC: 71101-201 | Form: GEL
Manufacturer: Veridian Healthcare
Category: otc | Type: HUMAN OTC DRUG LABEL
Date: 20241218

ACTIVE INGREDIENTS: BENZOCAINE 200 mg/1 g; BENZALKONIUM CHLORIDE 10 mg/1 g
INACTIVE INGREDIENTS: WATER; DIMETHYLHYDROXY FURANONE; SODIUM POLYACRYLATE (8000 MW); SACCHARIN SODIUM; SORBIC ACID; SORBITOL; GLYCERIN; POLYETHYLENE GLYCOL, UNSPECIFIED

TheraCare Maximum Strength Oral Pain Relief

Active ingredients

Benzocaine 20%

Benzalkonium Chloride 0.1%

Purpose

Oral pain reliever

Antiseptic

Use

- for the temporary relief of pain due to toothaches
- to help protect against infection in minor oral irritation

Warnings

Methemoglobinemia warning: use of this product may cause methemoglobinemia, a serious condition that must be treated promptly because it reduces the amount of oxygen carried in blood. This can occur even if you have used this product before. Stop use and seek immediate medical attention if you or a child in your care develops: ■ pale, gray or blue-colored skin (cyanosis) ■ headache ■ rapid heart rate ■ shortness of breath ■ dizziness or lightheadedness ■ fatigue or lack of energy

Allergy alert: do not use this product if you have a history of allergy to local anesthetics such as procaine, butacaine, benzocaine, or other "caine" anesthetics

Do not use

- more than directed
- for more than 7 days unless directed by a physician or healthcare provider

Stop use and ask a physician if

- swelling, rash or fever develops
- irritation, pain or redness persists or worsens
- symptoms do not improve in 7 days

KEEP OUT OF REACH OF CHILDREN:

In case of overdose or allergic reaction, get medical help or contact a Poison Control Center right away (1-800-222-1222)

Directions

- Adults and children 2 years of age and over - Apply a small amount of product to the cavity and around the gum surrounding the teeth. Use up to 4 times daily or as directed by a physician or healthcare provider
- Children under 12 years of age - Should be supervised in the use of this product
- Children under 2 years of age - Ask a physician or healthcare provider

Other information

- this preparation is intended for use in cases of toothache, only as a temporary expedient until a physician can be consulted
- do not use continuously
- avoid using toothpaste or drinking soft drinks or fruit juices for at least one hour after applying
- do not use if tube seal under cap is broken
- store at 20-25C (68-77F)

Inactive ingredients

Glycerin, polyethylene glycol, saccharin sodium, sodium polyacrylate, sorbic acid, sorbitol, strawberry furanone, water.

Questions or comments?

TOLL FREE 866-326-1313 M-F 8:30 am-4:30 pm CST